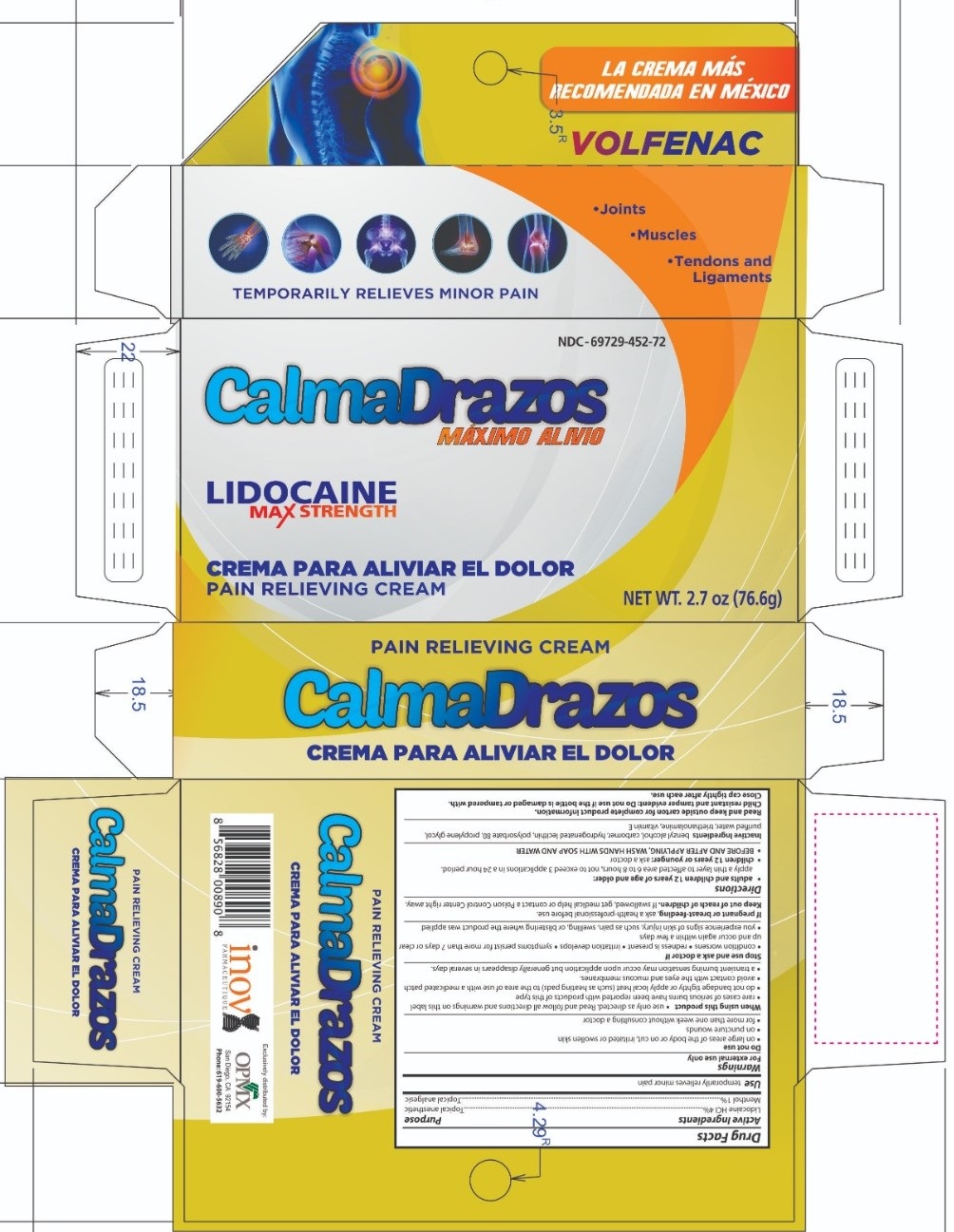 DRUG LABEL: Lidocaine HCl 4% Menthol 1%
NDC: 69729-452 | Form: OINTMENT
Manufacturer: OPMX LLC
Category: otc | Type: HUMAN OTC DRUG LABEL
Date: 20220610

ACTIVE INGREDIENTS: LIDOCAINE 4 g/100 g; MENTHOL 1 g/100 g
INACTIVE INGREDIENTS: .ALPHA.-TOCOPHEROL ACETATE; TROLAMINE; HYDROGENATED SOYBEAN LECITHIN; WATER; BENZYL ALCOHOL; CARBOMER 940; POLYSORBATE 80; PROPYLENE GLYCOL

CalmaDrazos
Lidocaine HCl 4% and Menthol 1%

ACTIVE INGREDIENT

Lidocaine HCl 4%

Menthol 1%

INACTIVE INGREDIENT

benzyl alcohol, carbomer, hydrogenated lecithin, polysorbate 80, propylene glycol, purified water triethanolamine, vitamin E

DOSAGE AND ADMINISTRATION

Adults and children 12 years and older: apply a thin layer to affected area every 6 to 8 hours, not to exceed 3 to 4 applications in a 24-hour period.

BEFORE AND AFTER APPLYING, WASH HANDS WITH SOAP AND WATER.

Children under 12 years: ask a doctor

INDICATIONS AND USAGE

temporary relieves minor pain

WARNINGS

For external use only

Do not use on large areas of the body or on cut, irritated or swollen skin, on puncture wounds, for more than one week without consulting a doctor.

When using this product use only as directed. Read and follow all directions and warnings on this label, rare cases of serious burns have been reported with products of this type, do not bandage or apply local heat (such as heating pads) to the area of use or use with a medicated, avoid contact with eyes and mucous membranes, a transient burning sensation may occur upon application but generally disappears in several days.

Stop use and ask a doctor if condition worsens, redness is present, irritation develops, symptoms persist for more than 7 days or clear up and occur again within a few days, you experience signs of skin injury, such as pain, swelling, or blistering where the product was applied.

If pregnant or breast-feeding, ask a health professional before use.

Keep out of reach of children and pets.

If swallowed, get medical help or contact a Poison Control Center right away.

PURPOSE

Topical anesthetic

Topical analgesic

PACKAGE LABEL

NDC: 69729-452-72 Calmadrazos